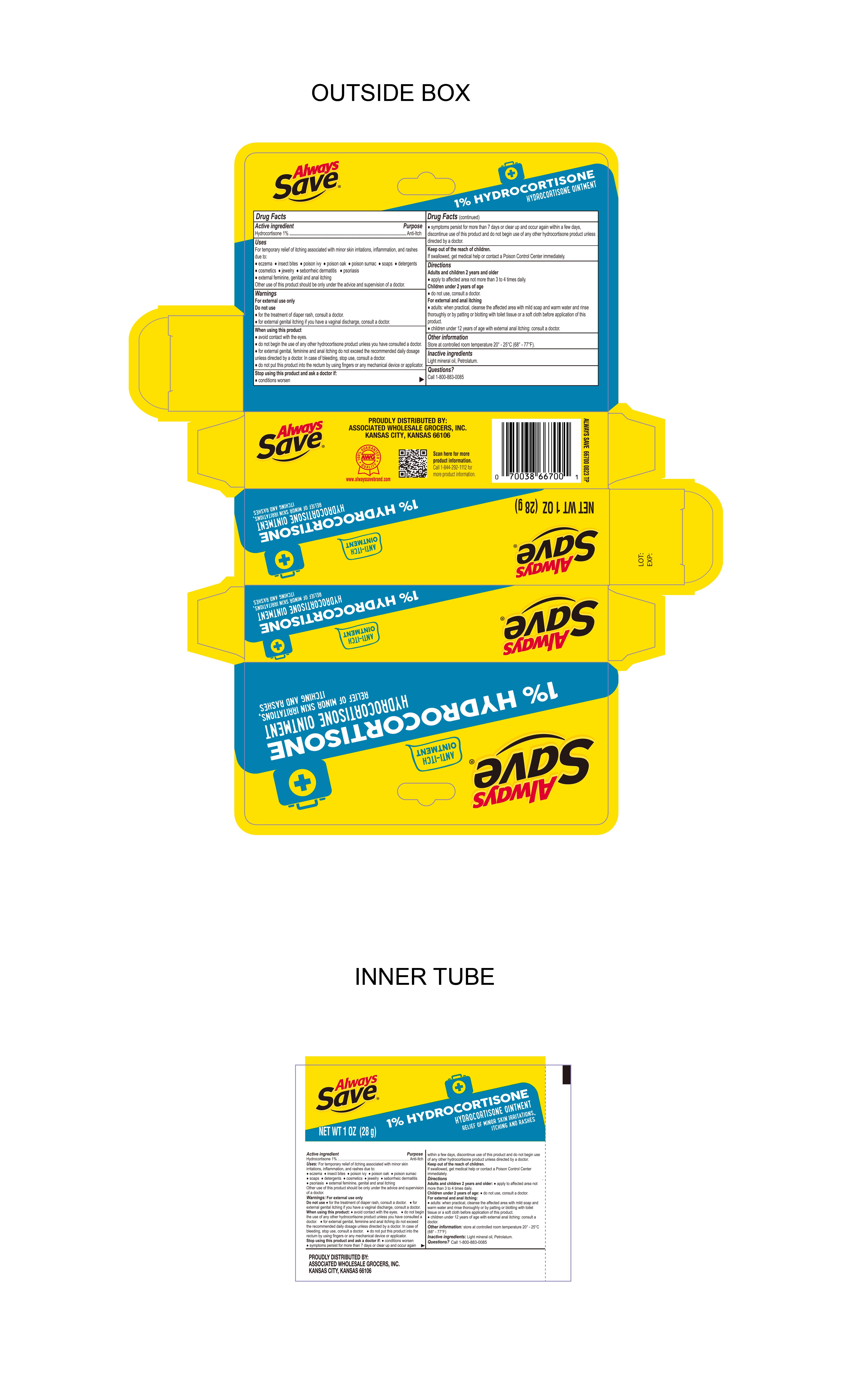 DRUG LABEL: Hydrocortisone
NDC: 69396-149 | Form: OINTMENT
Manufacturer: TRIFECTA PHARMACEUTICALS USA LLC
Category: otc | Type: HUMAN OTC DRUG LABEL
Date: 20240311

ACTIVE INGREDIENTS: HYDROCORTISONE 1 g/100 g
INACTIVE INGREDIENTS: LIGHT MINERAL OIL; PETROLATUM

Always Save Hydrocortisone OINTMENT 1%

Active ingredient

Hydrocortisone 1%

Purpose

Anti-itch

Keep out of the reach of children

If swallowed, get medical help or contact a Poison Control Center immediately.

Uses

temporary relief of itching associated with minor skin irritations, inflammation and rashes due to:
● eczema ● seborrheic dermatitis ● psoriasis ● insect bites ● poison ivy, oak, sumac ● soaps
●detergents ● cosmetics ● jewelry ●external feminine genital and anal itching
other uses of this product should be only under the advice and supervision of a doctor.

Warnings

● for external use only

Directions

Adults and children 2 years and older

- apply to affected area not more than 3 to 4 times daily

Children under 2 years of age:

- Do not use, consult a doctor

For External and anal itching:

Adults: When practical, cleanse the affected area with mild soap and warm water and rinse thoroughly or by patting or blotting with toilet tissue or a soft cloth before application of this product.

Children under 12 years of age with external anal itching: consult a doctor.

Inactive ingredients Light Mineral Oil, Petrolatum

Do Not Use

- For the treatment of diaper rash, consult a doctor
- for external genital itching if you have a vaginal discharge, consult a doctor.

Other Information

- store at controlled room temperature 20°-25°C (68°- 77°F)

Distributed By

Proudly Distributed By:

Associated Wholesale Grocers Inc.

Kansas City, Kansas 66106

Stop using this product and ask a doctor if

- Conidtions worsen
- Symptoms persist for more than 7 days or clear up and occur again within a few days, discontinue use of this product and do not begin use any other hydrocortisone product unless directed by a doctor.

When Using This Product

- Avoid contact with eyes
- Do not begin the use of any other hydrocortisone product unless you have consulted a doctor.
- For external genital, feminine and anal itching do not exceed the recommended daily dosage unless directed by a doctor.
- In case of bleeding, stop use, consult a doctor.
- Do not put this product into the rectum by using fingers or any mechanical device or applicator.

Questions:

Call 1-800-883-0085